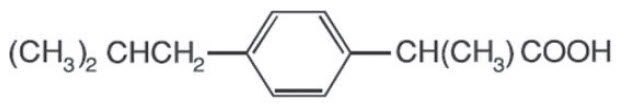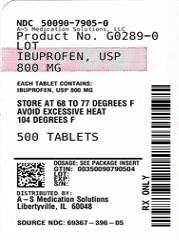 DRUG LABEL: Ibuprofen
NDC: 50090-7905 | Form: TABLET, FILM COATED
Manufacturer: A-S Medication Solutions
Category: prescription | Type: HUMAN PRESCRIPTION DRUG LABEL
Date: 20260217

ACTIVE INGREDIENTS: IBUPROFEN 800 mg/1 1
INACTIVE INGREDIENTS: SILICA; CROSCARMELLOSE SODIUM; MAGNESIUM STEARATE; CELLULOSE, MICROCRYSTALLINE; STARCH, CORN; POLYETHYLENE GLYCOL, UNSPECIFIED; SODIUM STARCH GLYCOLATE TYPE A POTATO; STEARIC ACID; TALC; TITANIUM DIOXIDE

Ibuprofen Tablets, USP 300 mg, 400 mg, 600 mg and 800 mg

BOXED WARNING

Cardiovascular Thrombotic Events

- Nonsteroidal anti-inflammatory drugs (NSAIDs) cause an increased risk of serious cardiovascular thrombotic events, including myocardial infarction and stroke, which can be fatal. This risk may occur early in treatment and may increase with duration of use. [See WARNINGS and PRECAUTIONS].
- Ibuprofen tablets are contraindicated in the setting of coronary artery bypass graft (CABG) surgery [see CONTRAINDICATIONS and WARNINGS].

Gastrointestinal Risk

- NSAIDS cause an increased risk of serious gastrointestinal adverse events including bleeding, ulceration, and perforation of the stomach or intestines, which can be fatal. These events can occur at any time during use and without warning symptoms. Elderly patients are at greater risk for serious gastrointestinal events. [See WARNINGS].

DESCRIPTION

Ibuprofen tablets, USP contain the active ingredient ibuprofen, which is (±) - 2 - (p - isobutylphenyl) propionic acid. Ibuprofen is a white powder with a melting point of 74-77°C and is very slightly soluble in water (<1 mg/mL) and readily soluble in organic solvents such as ethanol and acetone. The structural formula is represented below:

Ibuprofen, a nonsteroidal anti-inflammatory drug (NSAID), is available in 300 mg, 400 mg, 600 mg, and 800 mg tablets for oral administration. Inactive ingredients: colloidal silicon dioxide, croscarmellose sodium, magnesium stearate, microcrystalline cellulose, pregelatinized starch, polyethylene glycol, soidum starch glycoate, stearic acid, talc, titanium dioxide.

CLINICAL PHARMACOLOGY

Ibuprofen tablets contain ibuprofen which possesses analgesic and antipyretic activities. Its mode of action, like that of other NSAIDs, is not completely understood, but may be related to prostaglandin synthetase inhibition.

In clinical studies in patients with rheumatoid arthritis and osteoarthritis, Ibuprofen tablets have been shown to be comparable to aspirin in controlling pain and inflammation and to be associated with a statistically significant reduction in the milder gastrointestinal side effects [see ADVERSE REACTIONS]. Ibuprofen may be well tolerated in some patients who have had gastrointestinal side effects with aspirin, but these patients when treated with Ibuprofen tablets should be carefully followed for signs and symptoms of gastrointestinal ulceration and bleeding. Although it is not definitely known whether ibuprofen causes less peptic ulceration than aspirin, in one study involving 885 patients with rheumatoid arthritis treated for up to one year, there were no reports of gastric ulceration with ibuprofen whereas frank ulceration was reported in 13 patients in the aspirin group (statistically significant p<.001).

Gastroscopic studies at varying doses show an increased tendency toward gastric irritation at higher doses. However, at comparable doses, gastric irritation is approximately half that seen with aspirin. Studies using ^51Cr-tagged red cells indicate that fecal blood loss associated with Ibuprofen tablets in doses up to 2400 mg daily did not exceed the normal range, and was significantly less than that seen in aspirintreated patients.

In clinical studies in patients with rheumatoid arthritis, ibuprofen has been shown to be comparable to indomethacin in controlling the signs and symptoms of disease activity and to be associated with a statistically significant reduction of the milder gastrointestinal [see ADVERSE REACTIONS] and CNS side effects.

Ibuprofen may be used in combination with gold salts and/or corticosteroids.

Controlled studies have demonstrated that ibuprofen is a more effective analgesic than propoxyphene for the relief of episiotomy pain, pain following dental extraction procedures, and for the relief of the symptoms of primary dysmenorrhea.

In patients with primary dysmenorrhea, ibuprofen has been shown to reduce elevated levels of prostaglandin activity in the menstrual fluid and to reduce resting and active intrauterine pressure, as well as the frequency of uterine contractions. The probable mechanism of action is to inhibit prostaglandin synthesis rather than simply to provide analgesia.

Pharmacodynamics

In a healthy volunteer study, ibuprofen 400 mg given once daily, administered 2 hours prior to immediate-release aspirin (81 mg) for 6 days, showed an interaction with the antiplatelet activity of aspirin as measured by % serum thromboxane B2 (TxB2) inhibition at 24 hours following the day-6 aspirin dose [53%]. An interaction was still observed, but minimized, when ibuprofen 400 mg given once-daily was administered as early as 8 hours prior to the immediate-release aspirin dose [90.7%]. However, there was no interaction with the antiplatelet activity of aspirin when ibuprofen 400 mg, given once daily, was administered 2 hours after (but not concomitantly, 15 min, or 30 min after) the immediate-release aspirin dose [99.2%].

In another study, where immediate-release aspirin 81 mg was administered once daily with ibuprofen 400 mg given three times daily (1, 7, and 13 hours post-aspirin dose) for 10 consecutive days, the mean % serum thromboxane B2 (TxB2) inhibition suggested no interaction with the antiplatelet activity of aspirin [98.3%]. However, there were individual subjects with serum TxB2 inhibition below 95%, with the lowest being 90.2%.

When a similarly designed study was conducted with enteric-coated aspirin, where healthy subjects were administered enteric-coated aspirin 81 mg once daily for 6 days and ibuprofen 400 mg three times daily (2, 7 and 12 h post-aspirin dose) for 6 days, there was an interaction with the antiplatelet activity at 24 hours following the day-6 aspirin dose [67%]. [See Precautions/Drug Interactions].

Pharmacokinetics

The ibuprofen in Ibuprofen tablets is rapidly absorbed. Peak serum ibuprofen levels are generally attained one to two hours after administration. With single doses up to 800 mg, a linear relationship exists between amount of drug administered and the integrated area under the serum drug concentration vs time curve. Above 800 mg, however, the area under the curve increases less than proportional to increases in dose. There is no evidence of drug accumulation or enzyme induction.

The administration of Ibuprofen tablets either under fasting conditions or immediately before meals yields quite similar serum ibuprofen concentration-time profiles. When ibuprofen is administered immediately after a meal, there is a reduction in the rate of absorption but no appreciable decrease in the extent of absorption. The bioavailability of the drug is minimally altered by the presence of food.

A bioavailability study has shown that there was no interference with the absorption of ibuprofen when given in conjunction with an antacid containing both aluminum hydroxide and magnesium hydroxide.

Ibuprofen is rapidly metabolized and eliminated in the urine. The excretion of ibuprofen is virtually complete 24 hours after the last dose. The serum half-life is 1.8 to 2.0 hours.

Studies have shown that following ingestion of the drug, 45% to 79% of the dose was recovered in the urine within 24 hours as metabolite A (25%), (+)-2-[ p-(2hydroxymethyl-propyl) phenyl] propionic acid and metabolite B (37%), (+)-2-[ p-(2carboxypropyl)phenyl]propionic acid; the percentages of free and conjugated ibuprofen were approximately 1% and 14%, respectively.

INDICATIONS AND USAGE

Carefully consider the potential benefits and risks of Ibuprofen tablets and other treatment options before deciding to use ibuprofen. Use the lowest effective dose for the shortest duration consistent with individual patient treatment goals [see WARNINGS].

Ibuprofen tablets are indicated for relief of the signs and symptoms of rheumatoid arthritis and osteoarthritis.

Ibuprofen tablets are indicated for relief of mild to moderate pain. Ibuprofen tablets are also indicated for the treatment of primary dysmenorrhea.

Controlled clinical trials to establish the safety and effectiveness of Ibuprofen tablets in children have not been conducted.

CONTRAINDICATIONS

Ibuprofen tablets are contraindicated in patients with known hypersensitivity to ibuprofen.

Ibuprofen tablets should not be given to patients who have experienced asthma, urticaria, or allergic-type reactions after taking aspirin or other NSAIDs. Severe, rarely fatal, anaphylactic-like reactions to NSAIDs have been reported in such patients [see WARNINGS, Anaphylactoid Reactions, and PRECAUTIONS, Preexisting Asthma].

Ibuprofen tablets are contraindicated in the setting of coronary artery bypass graft (CABG) surgery [see WARNINGS].

WARNINGS

CARDIOVASCULAR EFFECTS

Cardiovascular Thrombotic Events

Clinical trials of several COX-2 selective and nonselective NSAIDs of up to three years duration have shown an increased risk of serious cardiovascular (CV) thrombotic events, including myocardial infarction (MI) and stroke, which can be fatal. Based on available data, it is unclear that the risk for CV thrombotic events is similar for all NSAIDs. The relative increase in serious CV thrombotic events over baseline conferred by NSAID use appears to be similar in those with and without known CV disease or risk factors for CV disease. However, Patients with known CV disease or risk factors had a higher absolute incidence of excess serious CV thrombotic events, due to their increased baseline rate. Some observational studies found that this increased risk of serious CV thrombotic events began as early as the first weeks of treatment. The increase in CV thrombotic risk has been observed most consistently at higher doses.

To minimize the potential risk for an adverse CV event in NSAID-treated patients, use the lowest effective dose for the shortest duration possible.

Physicians and patients should remain alert for the development of such events, throughout the entire treatment course, even in the absence of previous CV symptoms. Patients should be informed about the symptoms of serious CV events and the steps to take if they occur.

There is no consistent evidence that concurrent use of aspirin mitigates the increased risk of serious CV thrombotic events associated with NSAID use. The concurrent use of aspirin and an NSAID, such as Ibuprofen, increase the risk of serious gastrointestinal (GI) events [see WARNINGS].

Status Post Coronary Artery Bypass Graft (CABG) Surgery

Two large, controlled clinical trials of a COX-2 selective NSAID for the treatment of pain in the first 10-14 days following CABG surgery found an increased incidence of myocardial infarction and stroke. NSAIDs are contraindicated in the setting of CABG [see CONTRAINDICATIONS].

Post-MI Patients

Observational studies conducted in the Danish National Registry have demonstrated that patients treated with NSAIDs in the post-MI period were at increased risk of reinfarction, CV-related death, and all-cause mortality beginning in the first week of treatment. In this same cohort, the incidence of death in the first year post MI was 20 per 100 person years in NSAID-treated patients compared to 12 per 100 person years in non-NSAID exposed patients. Although the absolute rate of death declined somewhat after the first year post-MI, the increased relative risk of death in NSAID users persisted over at least the next four years of follow-up.

Avoid the use of Ibuprofen tablets in patients with a recent MI unless the benefits are expected to outweigh the risk of recurrent CV thrombotic events. If Ibuprofen tablets are used in patients with a recent MI, monitor patients for signs of cardiac ischemia.

Hypertension

NSAIDs including Ibuprofen tablets, can lead to onset of new hypertension or worsening of preexisting hypertension, either of which may contribute to the increased incidence of CV events. Patients taking thiazides or loop diuretics may have impaired response to these therapies when taking NSAIDs. NSAIDs, including Ibuprofen tablets, should be used with caution in patients with hypertension. Blood pressure (BP) should be monitored closely during the initiation of NSAID treatment and throughout the course of therapy.

Heart Failure and Edema

The Coxib and traditional NSAID Trialists' Collaboration meta-analysis of randomized controlled trials demonstrated an approximately two-fold increase in hospitalizations for heart failure in COX-2 selective-treated patients and nonselective NSAID-treated patients compared to placebotreated patients. In a Danish National Registry study of patients with heart failure, NSAID use increased the risk of MI, hospitalization for heart failure, and death.

Additionally, fluid retention and edema have been observed in some patients treated with NSAIDs. Use of Ibuprofen may blunt the CV effects of several therapeutic agents used to treat these medical conditions [e.g., diuretics, ACE inhibitors, or angiotensin receptor blockers (ARBs)] [See Drug Interactions].

Avoid the use of Ibuprofen tablets in patients with severe heart failure unless the benefits are expected to outweigh the risk of worsening heart failure. If Ibuprofen tablets are used in patients with severe heart failure, monitor patients for signs of worsening heart failure.

Gastrointestinal Effects - Risk of Ulceration, Bleeding, and Perforation

NSAIDs, including Ibuprofen tablets, can cause serious gastrointestinal (GI) adverse events including inflammation, bleeding, ulceration, and perforation of the stomach, small intestine, or large intestine, which can be fatal. These serious adverse events can occur at any time, with or without warning symptoms, in patients treated with NSAIDs. Only one in five patients, who develop a serious upper GI adverse event on NSAID therapy, is symptomatic. Upper GI ulcers, gross bleeding, or perforation caused by NSAIDs occur in approximately 1% of patients treated for 3-6 months, and in about 2-4% of patients treated for one year. These trends continue with longer duration of use, increasing the likelihood of developing a serious GI event at some time during the course of therapy. However, even short-term therapy is not without risk. NSAIDs should be prescribed with extreme caution in those with a prior history of ulcer disease or gastrointestinal bleeding. Patients with a prior history of peptic ulcer disease and/or gastrointestinal bleeding who use NSAIDs have a greater than 10-fold increased risk for developing a GI bleed compared to patients treated with neither of these risk factors. Other factors that increase the risk of GI bleeding in patients treated with NSAIDs include concomitant use of oral corticosteroids or anticoagulants, longer duration of NSAID therapy, smoking, use of alcohol, older age, and poor general health status. Most spontaneous reports of fatal GI events are in elderly or debilitated patients and therefore, special care should be taken in treating this population. To minimize the potential risk for an adverse GI event in patients treated with a NSAID, the lowest effective dose should be used for the shortest possible duration. Patients and physicians should remain Alert for signs and symptoms of GI ulcerations and bleeding during NSAID therapy and promptly initiate additional evaluation and treatment if a serious GI event is suspected. This should include discontinuation of the NSAID until a serious GI adverse event is ruled out. For high-risk patients, alternate therapies that do not involve NSAIDs should be considered.

Renal Effects

Long-term administration of NSAIDs has resulted in renal papillary necrosis and other renal injury. Renal toxicity has also been seen in patients in whom renal prostaglandins have a compensatory role in the maintenance of renal perfusion. In these patients, administration of a NSAID may cause a dose dependent reduction in prostaglandin formation and, secondarily, in renal blood flow, which may precipitate overt renal decompensation. Patients at greatest risk of this reaction are those with impaired renal function, heart failure, liver dysfunction, those taking diuretics and ACE inhibitors, and the elderly. Discontinuation of NSAID therapy is usually followed by recovery to the pretreatment state.

Advanced Renal Disease

No information is available from controlled clinical studies regarding the use of Ibuprofen tablets in patients with advanced renal disease. Therefore, treatment with Ibuprofen tablets is not recommended in these patients with advanced renal disease. If Ibuprofen tablet therapy must be initiated, close monitoring of the patients renal function is advisable.

Anaphylactoid Reactions

As with other NSAIDs, anaphylactoid reactions may occur in patients without known prior exposure to Ibuprofen tablets. Ibuprofen tablets should not be given to patients with the aspirin triad. This symptom complex typically occurs in asthmatic patients who experience rhinitis with or without nasal polyps, or who exhibit severe, potentially fatal bronchospasm after taking aspirin or other NSAIDs [see CONTRAINDICATIONS and PRECAUTIONS, Preexisting Asthma]. Emergency help should be sought in cases where an anaphylactoid reaction occurs.

Serious Skin Reactions

NSAIDs, including Ibuprofen, can cause serious skin adverse reactions such as exfoliative dermatitis, Stevens-Johnson Syndrome (SJS), and toxic epidermal necrolysis (TEN), which can be fatal. NSAIDs can also cause fixed drug eruption (FDE). FDE may present as a more severe variant known as generalized bullous fixed drug eruption (GBFDE), which can be life-threatening. These serious events may occur without warning. Inform patients about the signs and symptoms of serious skin reactions, and to discontinue the use of Ibuprofen tablets at the first appearance of skin rash or any other sign of hypersensitivity. Ibuprofen tablets are contraindicated in patients with previous serious skin reactions to NSAIDs (see CONTRAINDICATIONS).

Drug Reaction with Eosinophilia and Systemic Symptoms (DRESS) has been reported in patients taking NSAIDs such as Ibuprofen tablets. Some of these events have been fatal or life-threatening. DRESS typically, although not exclusively, presents with fever, rash, lymphadenopathy, and/or facial swelling. Other clinical manifestations may include hepatitis, nephritis, hematological abnormalities, myocarditis, or myositis. Sometimes symptoms of DRESS may resemble an acute viral infection. Eosinophilia is often present.

Because this disorder is variable in its presentation, other organ systems not noted here may be involved. It is important to note that early manifestations of hypersensitivity, such as fever or lymphadenopathy, may be present even though rash is not evident. If such signs or symptoms are present, discontinue Ibuprofen tablets and evaluate the patient immediately.

Fetal Toxicity

Premature Closure of Fetal Ductus Arteriosus

Avoid use of NSAIDs, including Ibuprofen tablets, in pregnant women at about 30 weeks gestation and later. NSAIDs including Ibuprofen tablets, increase the risk of premature closure of the fetal ductus arteriosus at approximately this gestational age.

Oligohydramnios/Neonatal Renal Impairment

Use of NSAIDs, including Ibuprofen tablets, at about 20 weeks gestation or later in pregnancy may cause fetal renal dysfunction leading to oligohydramnios and, in some cases, neonatal renal impairment. These adverse outcomes are seen, on average, after days to weeks of treatment, although oligohydramnios has been infrequently reported as soon as 48 hours after NSAID initiation.

Oligohydramnios is often, but not always, reversible with treatment discontinuation. Complications of prolonged oligohydramnios may, for example, include limb contractures and delayed lung maturation. In some postmarketing cases of impaired neonatal renal function, invasive procedures such as exchange transfusion or dialysis were required.

If NSAID treatment is necessary between about 20 weeks and 30 weeks gestation, limit Ibuprofen tablets use to the lowest effective dose and shortest duration possible. Consider ultrasound monitoring of amniotic fluid if Ibuprofen tablets treatment extends beyond 48 hours.

Discontinue Ibuprofen tablets if oligohydramnios occurs and follow up according to clinical practice [see PRECAUTIONS; Pregnancy].

PRECAUTIONS

General

Ibuprofen tablets cannot be expected to substitute for corticosteroids or to treat corticosteroid insufficiency. Abrupt discontinuation of corticosteroids may lead to disease exacerbation. Patients on prolonged corticosteroid therapy should have their therapy tapered slowly if a decision is made to discontinue corticosteroids.

The pharmacological activity of Ibuprofen tablets in reducing fever and inflammation may diminish the utility of these diagnostic signs in detecting complications of presumed noninfectious, painful conditions.

Hepatic effects

Borderline elevations of one or more liver tests may occur in up to 15% of patients taking NSAIDs, including Ibuprofen tablets. These laboratory abnormalities may progress, may remain unchanged, or may be transient with continuing therapy. Notable elevations of ALT or AST (approximately three or more times the upper limit of normal) have been reported in approximately 1% of patients in clinical trials with NSAIDs.

In addition, rare cases of severe hepatic reactions, including jaundice, fulminant hepatitis, liver necrosis, and hepatic failure, some of them with fatal outcomes have been reported. A patient with symptoms and/ or signs suggesting liver dysfunction, or with abnormal liver test values, should be evaluated for evidence of the development of a more severe hepatic reaction while on therapy with Ibuprofen tablets. If clinical signs and symptoms consistent with liver disease develop, or if systemic manifestations occur (e.g., eosinophilia, rash, etc.), Ibuprofen tablets should be discontinued.

Hematological effects

Anemia is sometimes seen in patients receiving NSAIDs, including Ibuprofen tablets. This may be due to fluid retention, occult or gross GI blood loss, or an incompletely described effect upon erythropoiesis. Patients on long-term treatment with NSAIDs, including Ibuprofen tablets, should have their hemoglobin or hematocrit checked if they exhibit any signs or symptoms of anemia.

In two postmarketing clinical studies the incidence of a decreased hemoglobin level was greater than previously reported. Decrease in hemoglobin of 1 gram or more was observed in 17.1% of 193 patients on 1600 mg ibuprofen daily (osteoarthritis), and in 22.8% of 189 patients taking 2400 mg of ibuprofen daily (rheumatoid arthritis). Positive stool occult blood tests and elevated serum creatinine levels were also observed in these studies.

NSAIDs inhibit platelet aggregation and have been shown to prolong bleeding time in some patients. Unlike aspirin, their effect on platelet function is quantitatively less, of shorter duration, and reversible. Patients receiving Ibuprofen tablets who may be adversely affected by alterations in platelet function, such as those with coagulation disorders or patients receiving anticoagulants should be carefully monitored.

Preexisting asthma

Patients with asthma may have aspirin-sensitive asthma. The use of aspirin in patients with aspirin-sensitive asthma has been associated with severe bronchospasm, which can be fatal. Since cross reactivity, including bronchospasm, between aspirin and NSAIDs has been reported in such aspirin-sensitive patients, Ibuprofen tablets should not be administered to patients with this form of aspirin sensitivity and should be used with caution in patients with preexisting asthma.

Ophthalmological effects

Blurred and/or diminished vision, scotomata, and/or changes in color vision have been reported. If a patient develops such complaints while receiving Ibuprofen tablets, the drug should be discontinued, and the patient should have an ophthalmologic examination which includes central visual fields and color vision testing.

Aseptic Meningitis

Aseptic meningitis with fever and coma has been observed on rare occasions in patients on ibuprofen therapy. Although it is probably more likely to occur in patients with systemic lupus erythematosus and related connective tissue diseases, it has been reported in patients who do not have an underlying chronic disease. If signs or symptoms of meningitis develop in a patient on Ibuprofen tablets, the possibility of its being related to Ibuprofen tablets should be considered.

Information for Patients

Patients should be informed of the following information before initiating therapy with an NSAID and periodically during the course of ongoing therapy. Patients should also be encouraged to read the NSAID Medication Guide that accompanies each prescription dispensed.

- CARDIOVASCULAR THROMBOTIC EVENTS Advise patients to be alert for the symptoms of cardiovascular thrombotic events, including chest pain, shortness of breath, weakness, or slurring of speech, and to report any of these symptoms to their health care provider immediately [see WARNINGS].
- Ibuprofen tablets, like other NSAIDs, can cause GI discomfort and, rarely, serious GI side effects, such as ulcers and bleeding, which may result in hospitalization and even death. Although serious GI tract ulcerations and bleeding can occur without warning symptoms, patients should be alert for the signs and symptoms of ulcerations and bleeding, and should ask for medical advice when observing any indicative signs or symptoms including epigastric pain, dyspepsia, melena, and hematemesis. Patients should be apprised of the importance of this follow-up [see WARNINGS, Gastrointestinal Effects-Risk of Ulceration, Bleeding and Perforation].
- Serious Skin Reactions, including DRESS: Advise patients to stop taking Ibuprofen tablets immediately if they develop any type of rash or fever and to contact their healthcare provider as soon as possible [see WARNINGS].
- Heart failure and Edema: Advise patients to be alert for the symptoms of congestive heart failure including shortness of breath, unexplained weight gain, or edema and to contact their healthcare provider if such symptoms occur [see WARNINGS].
- Patients should be informed of the warning signs and symptoms of hepatotoxicity (e.g., nausea, fatigue, lethargy, pruritus, jaundice, right upper quadrant tenderness and "flu-like" symptoms). If these occur, patients should be instructed to stop therapy and seek immediate medical therapy.
- Patients should be informed of the signs of an anaphylactoid reaction (e.g. difficulty breathing, swelling of the face or throat). If these occur, patients should be instructed to seek immediate emergency help [see WARNINGS].
- In late pregnancy, as with other NSAIDs, Ibuprofen tablets should be avoided because it may cause premature closure of the ductus arteriosus.

Fetal Toxicity

Inform pregnant women to avoid use of Ibuprofen tablets and other NSAIDs starting at 30 weeks gestation because of the risk of the premature closing of the fetal ductus arteriosus. If treatment with Ibuprofen tablets is needed for a pregnant woman between about 20 to 30 weeks gestation, advise her that she may need to be monitored for oligohydramnios, if treatment continues for longer than 48 hours [see WARNINGS; Fetal Toxicity, PRECAUTIONS; Pregnancy].

Laboratory Tests

Because serious GI tract ulcerations and bleeding can occur without warning symptoms, physicians should monitor for signs or symptoms of GI bleeding. Patients on long-term treatment with NSAIDs should have their CBC and chemistry profile checked periodically. If clinical signs and symptoms consistent with liver or renal disease develop, systemic manifestations occur (e.g., eosinophilia, rash, etc.), or abnormal liver tests persist or worsen, Ibuprofen tablets should be discontinued.

Drug Interactions

ACE-inhibitors

Reports suggest that NSAIDs may diminish the antihypertensive effect of ACE-inhibitors. This interaction should be given consideration in patients taking NSAIDs concomitantly with ACE-inhibitors.

Aspirin

Pharmacodynamic studies have demonstrated interference with the antiplatelet activity of aspirin when ibuprofen 400 mg, given three times daily, is administered with enteric-coated low-dose aspirin. The interaction exists even following a once-daily regimen of ibuprofen 400 mg, particularly when ibuprofen is dosed prior to aspirin. The interaction is alleviated if immediate-release low-dose aspirin is dosed at least 2 hours prior to a once-daily regimen of ibuprofen; however, this finding cannot be extended to enteric-coated low-dose aspirin [see Clinical Pharmacology/Pharmacodynamics].

Because there may be an increased risk of cardiovascular events due to the interference of ibuprofen with the antiplatelet effect of aspirin, for patients taking low-dose aspirin for cardio protection who require analgesics, consider use of a NSAID that does not interfere with the antiplatelet effect of aspirin, or non-NSAID analgesics, where appropriate.

When Ibuprofen tablets are administered with aspirin, its protein binding is reduced, although the clearance of free Ibuprofen tablets is not altered. The clinical significance of this interaction is not known; however, as with other NSAIDs, concomitant administration of ibuprofen and aspirin is not generally recommended because of the potential for increased adverse effects.

Diuretics

Clinical studies, as well as post marketing observations, have shown that Ibuprofen tablets can reduce the natriuretic effect-of furosemide and thiazides in some patients. This response has been attributed to inhibition of renal prostaglandin synthesis. During concomitant therapy with NSAIDs, the patient should be observed closely for signs of renal failure [see PRECAUTIONS, Renal Effects], as well as to assure diuretic efficacy.

Lithium

Ibuprofen produced an elevation of plasma lithium levels and a reduction in renal lithium clearance in a study of eleven normal volunteers. The mean minimum lithium concentration increased 15% and the renal clearance of lithium was decreased by 19% during this period of concomitant drug administration.

This effect has been attributed to inhibition of renal prostaglandin synthesis by ibuprofen. Thus, when ibuprofen and lithium are administered concurrently, subjects should be observed carefully for signs of lithium toxicity. (Read circulars for lithium preparation before use of such concurrent therapy.)

Methotrexate

NSAIDs have been reported to competitively inhibit methotrexate accumulation in rabbit kidney slices. This may indicate that they could enhance the toxicity of methotrexate. Caution should be used when NSAIDs are administered concomitantly with methotrexate.

Warfarin-type anticoagulants

Several short-term controlled studies failed to show that Ibuprofen tablets significantly affected prothrombin times or a variety of other clotting factors when administered to individuals on coumarin-type anticoagulants. However, because bleeding has been reported when Ibuprofen tablets and other NSAIDs have been administered to patients on coumarin-type anticoagulants, the physician should be cautious when administering Ibuprofen tablets to patients on anticoagulants. The effects of warfarin and NSAIDs on GI bleeding are synergistic, such that the users of both drugs together have a risk of serious GI bleeding higher than users of either drug alone.

H-2 Antagonists

In studies with human volunteers, co-administration of cimetidine or ranitidine with ibuprofen had no substantive effect on ibuprofen serum concentrations.

Pregnancy

Risk Summary

Use of NSAIDs, including Ibuprofen tablets, can cause premature closure of the fetal ductus arteriosus and fetal renal dysfunction leading to oligohydramnios and, in some cases, neonatal renal impairment. Because of these risks, limit dose and duration of Ibuprofen tablets use between about 20 and 30 weeks of gestation, and avoid Ibuprofen tablets use at about 30 weeks of gestation and later in pregnancy [see WARNINGS; Fetal Toxicity].

Premature Closure of Fetal Ductus Arteriosus

Use of NSAIDs, including Ibuprofen tablets, at about 30 weeks gestation or later in pregnancy increases the risk of premature closure of the fetal ductus arteriosus.

Oligohydramnios/Neonatal Renal Impairment

Use of NSAIDs at about 20 weeks gestation or later in pregnancy has been associated with cases of fetal renal dysfunction leading to oligohydramnios, and in some cases, neonatal renal impairment.

Data from observational studies regarding other potential embryofetal risks of NSAID use in women in the first or second trimesters of pregnancy are inconclusive. Reproductive studies conducted in rats and rabbits have not demonstrated evidence of developmental abnormalities. However, animal reproduction studies are not always predictive of human response. Based on animal data, prostaglandins have been shown to have an important role in endometrial vascular permeability, blastocyst implantation, and decidualization. In animal studies, administration of prostaglandin synthesis inhibitors such as Ibuprofen, resulted in increased pre- and post-implantation loss. Prostaglandins also have been shown to have an important role in fetal kidney development. In published animal studies, prostaglandin synthesis inhibitors have been reported to impair kidney development when administered at clinically relevant doses.

The estimated background risk of major birth defects and miscarriage for the indicated population(s) is unknown. All pregnancies have a background risk of birth defect, loss, or other adverse outcomes. In the U.S. general population, the estimated background risk of major birth defects and miscarriage in clinically recognized pregnancies is 2-4% and 15-20%, respectively.

Clinical Considerations

Fetal/Neonatal Adverse Reactions

Premature Closure of Fetal Ductus Arteriosus: Avoid use of NSAIDs in women at about 30 weeks gestation and later in pregnancy, because NSAIDs, including Ibuprofen tablets, can cause premature closure of the fetal ductus arteriosus [see WARNINGS; Fetal Toxicity].

Oligohydramnios/Neonatal Renal Impairment

If an NSAID is necessary at about 20 weeks gestation or later in pregnancy, limit the use to the lowest effective dose and shortest duration possible. If Ibuprofen tablets treatment extends beyond 48 hours, consider monitoring with ultrasound for oligohydramnios. If oligohydramnios occurs, discontinue Ibuprofen tablets and follow up according to clinical practice [see WARNINGS; Fetal Toxicity].

Data

Human Data

There are no adequate, well-controlled studies in pregnant women. Ibuprofen tablets should be used in pregnancy only if the potential benefit justifies the potential risk to the fetus.

Premature Closure of Fetal Ductus Arteriosus

Published literature reports that the use of NSAIDs at about 30 weeks of gestation and later in pregnancy may cause premature closure of the fetal ductus arteriosus.

Oligohydramnios/Neonatal Renal Impairment

Published studies and postmarketing reports describe maternal NSAID use at about 20 weeks gestation or later in pregnancy associated with fetal renal dysfunction leading to oligohydramnios, and in some cases, neonatal renal impairment. These adverse outcomes are seen, on average, after days to weeks of treatment, although oligohydramnios has been infrequently reported as soon as 48 hours after NSAID initiation. In many cases, but not all, the decrease in amniotic fluid was transient and reversible with cessation of the drug. There have been a limited number of case reports of maternal NSAID use and neonatal renal dysfunction without oligohydramnios, some of which were irreversible. Some cases of neonatal renal dysfunction required treatment with invasive procedures, such as exchange transfusion or dialysis.

Methodological limitations of these postmarketing studies and reports include lack of a control group; limited information regarding dose, duration, and timing of drug exposure; and concomitant use of other medications. These limitations preclude establishing a reliable estimate of the risk of adverse fetal and neonatal outcomes with maternal NSAID use. Because the published safety data on neonatal outcomes involved mostly preterm infants, the generalizability of certain reported risks to the full-term infant exposed to NSAIDs through maternal use is uncertain.

Labor and Delivery

In rat studies with NSAIDs, as with other drugs known to inhibit prostaglandin synthesis, an increased incidence of dystocia, delayed parturition, and decreased pup survival occurred. The effects of Ibuprofen tablets on labor and delivery in pregnant women are unknown.

Nursing Mothers

It is not known whether this drug is excreted in human milk. Because many drugs are excreted in human-milk and because of the potential for serious adverse reactions in nursing infants from Ibuprofen tablets, a decision should be made whether to discontinue nursing or discontinue the drug, taking into account the importance of the drug to the mother.

Pediatric Use

Safety and effectiveness of Ibuprofen tablets in pediatric patients have not been established.

Geriatric Use

As with any NSAIDs, caution should be exercised in treating the elderly (65 years and older).

ADVERSE REACTIONS

The most frequent type of adverse reaction occurring with Ibuprofen tablets is gastrointestinal. In controlled clinical trials the percentage of patients reporting one or more gastrointestinal complaints ranged from 4% to 16%.

In controlled studies when Ibuprofen tablets were compared to aspirin and indomethacin in equally effective doses, the overall incidence of gastrointestinal complaints was about half that seen in either the aspirin- or indomethacin-treated patients.

Adverse reactions observed during controlled clinical trials at an incidence greater than 1% are listed in the table. Those reactions listed in Column one encompass observations in approximately 3,000 patients. More than 500 of these patients were treated for periods of at least 54 weeks.

Still other reactions occurring less frequently than 1 in 100 were reported in controlled clinical trials and from marketing experience. These reactions have been divided into two categories: Column two of the table lists reactions with therapy with Ibuprofen tablets where the probability of a causal relationship exists: for the reactions in Column three, a causal relationship with Ibuprofen tablets has not been established.

Reported side effects were higher at doses of 3200 mg/day than at doses of 2400 mg or less per day in clinical trials of patients with rheumatoid arthritis. The increases in incidence were slight and still within the ranges reported in the table.

Incidence Greater than 1% (but less than 3%) Probable Causal Relationship [Reactions occurring in 3% to 9% of patients treated with ibuprofen tablets. (Those reactions occurring in less than 3% of the patients are unmarked.)] | Precise Incidence Unknown (but less than 1%) Probable Causal Relationship [Reactions are classified under "Probable Causal Relationship (PCR)" if there has been one positive rechallenge or if three or more cases occur which might be causally related. Reactions are classified under "Causal Relationship Unknown" if seven or more events have been reported but the criteria for PCR have not been met.] | Precise Incidence Unknown (but less than 1%) Causal Relationship Unknown
GASTROINTESTINAL Nausea, epigastric pain, heartburn, diarrhea, abdominal distress, nausea and vomiting, indigestion, constipation, abdominal cramps or Pain, fullness of GI tract (bloating or flatulence) | Gastric or duodenal ulcer with bleeding and/or perforation, gastrointestinal hemorrhage, melena, gastritis, hepatitis, jaundice, abnormal liver function tests; pancreatitis
CENTRAL NERVOUS SYSTEM Dizziness, headache, nervousness | Depression, insomnia, confusion, emotional liability, somnolence, aseptic meningitis with fever and coma (see PRECAUTIONS) | Paresthesias, hallucinations, dream abnormalities, pseudotumor cerebri
DERMATOLOGIC Rash, (including maculopapular type), pruritus | Vesiculobullous eruptions, urticaria, erythema multiforme, Stevens-Johnson syndrome, alopecia | Toxic epidermal necrolysis, photoallergic skin reactions
SPECIAL SENSES Tinnitus | Hearing loss, amblyopia (blurred and/or diminished vision, scotomata and/or changes in color vision) (see PRECAUTIONS) | Conjunctivitis, diplopia, optic neuritis, cataracts
HEMATOLOGIC | Neutropenia, agranulocytosis, aplastic anemia, hemolytic anemia (sometimes Coombs positive), thrombocytopenia with or without purpura, eosinophilia, decreases in hemoglobin and hematocrit (see PRECAUTIONS) | Bleeding episodes (eg epistaxis, menorrhagia)
METABOLIC/ ENDOCRINE Decreased appetite |  | Gynecomastia, hypoglycemic reaction, acidosis
CARDIOVASCULAR Edema, fluid retention (generally responds promptly to drug discontinuation) (see PRECAUTIONS) | Congestive heart failure in patients with marginal cardiac function, elevated blood pressure, palpitations | Arrhythmias (sinus tachycardia, sinus bradycardia)
ALLERGIC | Syndrome of abdominal pain, fever, chills, nausea and vomiting; anaphylaxis; bronchospasm (see CONTRAINDICATIONS) | Serum sickness, lupus erythematosus syndrome. Henoch- Schonlein vasculitis, angioedema
RENAL | Acute renal failure (see PRECAUTIONS), decreased creatinine clearance, poliuria, azotemia, cystitis, Hematuria | Renal papillary necrosis
MISCELLANEOUS | Dry eyes and mouth, gingival ulcer, rhinitis

Postmarketing Experience

The following adverse reactions have been identified during postapproval use of ibuprofen. Because these reactions are reported voluntarily from a population of uncertain size, it is not always possible to reliably estimate their frequency or establish a causal relationship to drug exposure. Skin and Appendages: Exfoliative dermatitis, Stevens- Johnson Syndrome (SJS), toxic epidermal necrolysis (TEN), and fixed drug eruption (FDE).

OVERDOSAGE

Approximately 1½ hours after the reported ingestion of from 7 to 10 Ibuprofen tablets (400 mg), a 19-month old child weighing 12 kg was seen in the hospital emergency room, apneic and cyanotic, responding only to painful stimuli. This type of stimulus, however, was sufficient to induce respiration. Oxygen and parenteral fluids were given; a greenish-yellow fluid was aspirated from the stomach with no evidence to indicate the presence of ibuprofen. Two hours after ingestion the child's condition seemed stable; she still responded only to painful stimuli and continued to have periods of apnea lasting from 5 to 10 seconds. She was admitted to intensive care and sodium bicarbonate was administered as well as infusions of dextrose and normal saline.

By four hours post-ingestion she could be aroused easily, sit by herself and respond to spoken commands. Blood level of ibuprofen was 102.9 mcg/mL approximately 8½ hours after accidental ingestion. At 12 hours she appeared to be completely recovered.

In two other reported cases where children (each weighing approximately 10 kg) accidentally, acutely ingested approximately 120 mg/kg, there were no signs of acute intoxication or late sequelae. Blood level in one child 90 minutes after ingestion was 700 mcg/mL -- about 10 times the peak levels seen in absorption-excretion studies.

A 19-year old male who had taken 8,000 mg of ibuprofen over a period of a few hours complained of dizziness, and nystagmus was noted. After hospitalization, parenteral hydration and three days bed rest, he recovered with no reported sequelae.

In cases of acute overdosage, the stomach should be emptied by vomiting or lavage, though little drug will likely be recovered if more than an hour has elapsed since ingestion. Because the drug is acidic and is excreted in the urine, it is theoretically beneficial to administer alkali and induce diuresis. In addition to supportive measures, the use of oral activated charcoal may help to reduce the absorption and reabsorption of Ibuprofen tablets.

DOSAGE AND ADMINISTRATION

Carefully consider the potential benefits and risks of Ibuprofen Tablets, USP and other treatment options before deciding to use Ibuprofen Tablets, USP. Use the lowest effective dose for the shortest duration consistent with individual patient treatment goals [see WARNINGS].

After observing the response to initial therapy with Ibuprofen Tablets, USP, the dose and frequency should be adjusted to suit an individual patient's needs.

Do not exceed 3200 mg total daily dose. If gastrointestinal complaints occur, administer Ibuprofen tablets with meals or milk.

Rheumatoid arthritis and osteoarthritis, including flare-ups of chronic disease

Suggested Dosage: 1200 mg-3200 mg daily (400 mg, 600 mg or 800 mg tid or qid). Individual patients may show a better response to 3200 mg daily, as compared with 2400 mg, although in well-controlled clinical trials patients on 3200 mg did not show a better mean response in terms of efficacy. Therefore, when treating patients with 3200 mg/ day, the physician should observe sufficient increased clinical benefits to offset potential increased risk.

The dose should be tailored to each patient, and may be lowered or raised depending on the severity of symptoms either at time of initiating drug therapy or as the patient responds or fails to respond.

In general, patients with rheumatoid arthritis seem to require higher doses of Ibuprofen tablets than do patients with osteoarthritis.

The smallest dose of Ibuprofen tablets that yields acceptable control should be employed. A linear blood level dose-response relationship exists with single doses up to 800 mg [See CLINICAL PHARMACOLOGY for effects of food on rate of absorption].

The availability of three tablet strengths facilitates dosage adjustment.

In chronic conditions, a therapeutic response to therapy with Ibuprofen tablets is sometimes seen in a few days to a week but most often is observed by two weeks. After a satisfactory response has been achieved, the patient's dose should be reviewed and adjusted as required.

Mild to moderate pain

400 mg every 4 to 6 hours as necessary for relief of pain.

In controlled analgesic clinical trials, doses of Ibuprofen tablets greater than 400 mg were no more effective than the 400 mg dose.

Dysmenorrhea

For the treatment of dysmenorrhea, beginning with the earliest onset of such pain, Ibuprofen tablets should be given in a dose of 400 mg every 4 hours as necessary for the relief of pain.

HOW SUPPLIED

Product: 50090-7905

NDC: 50090-7905-0 500 TABLET, FILM COATED in a BOTTLE

Manufactured by:
Shandong Xinhua Pharmaceutical Co., Ltd.
No. 1 Lutai Road, High-tech District,
Zibo, Shandong, 255086, P.R. China
Manufactured for:
Westminster Pharmaceuticals, LLC
Nashville, TN 37217
LB8071
R0924